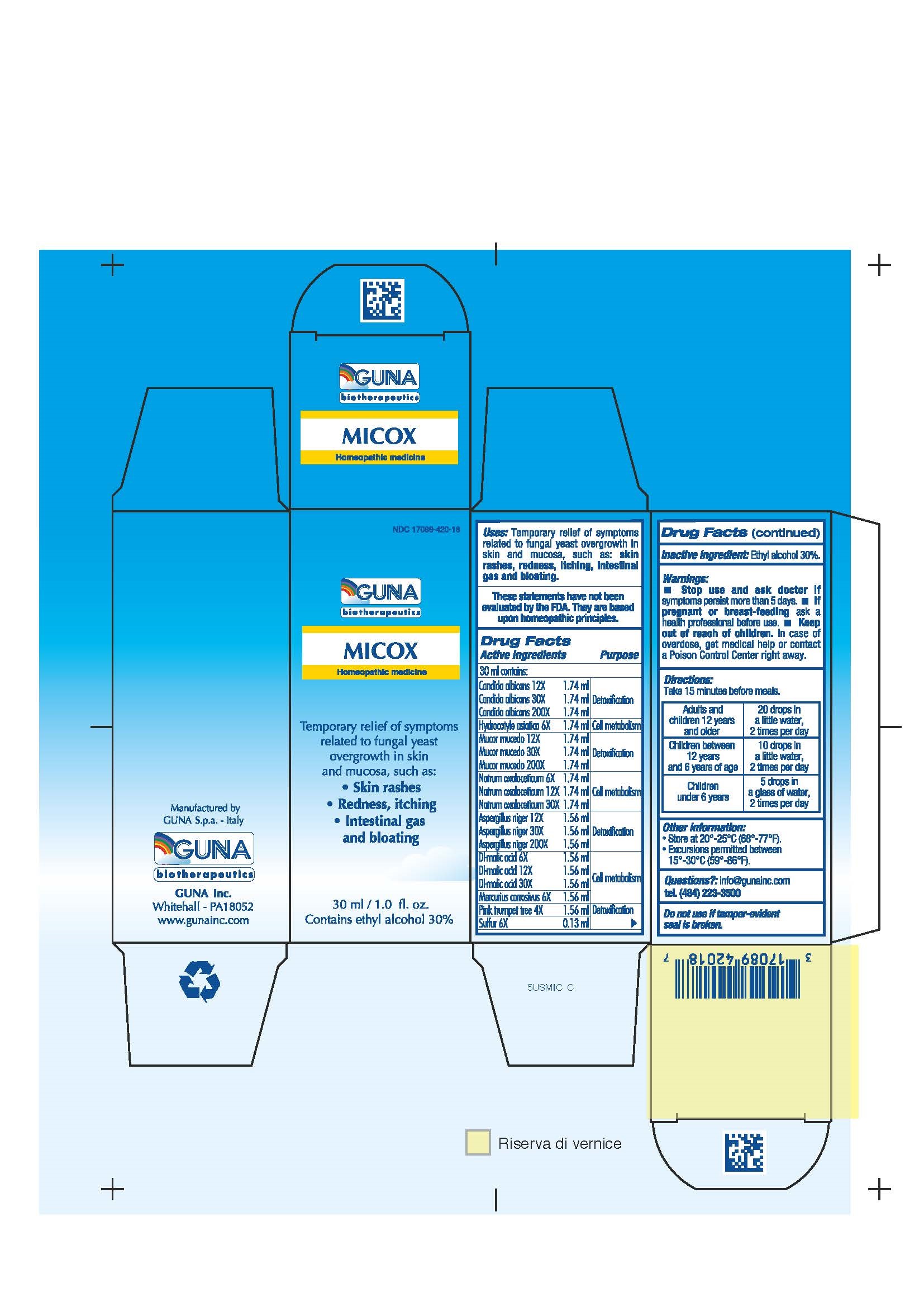 DRUG LABEL: MICOX
NDC: 17089-420 | Form: SOLUTION/ DROPS
Manufacturer: Guna spa
Category: homeopathic | Type: HUMAN OTC DRUG LABEL
Date: 20221115

ACTIVE INGREDIENTS: ASPERGILLUS NIGER VAR. NIGER 30 [hp_X]/30 mL; CANDIDA ALBICANS 30 [hp_X]/30 mL; MALIC ACID 12 [hp_X]/30 mL; CENTELLA ASIATICA 6 [hp_X]/30 mL; MERCURIC CHLORIDE 6 [hp_X]/30 mL; RHIZOPUS STOLONIFER 30 [hp_X]/30 mL; SODIUM DIETHYL OXALACETATE 12 [hp_X]/30 mL; TABEBUIA IMPETIGINOSA BARK 4 [hp_X]/30 mL; SULFUR 6 [hp_X]/30 mL
INACTIVE INGREDIENTS: ALCOHOL 9 mL/30 mL

MICOX

ACTIVE INGREDIENTS/PURPOSE

ASPERGILLUS NIGER 12X, 30X, 200X DETOXIFICATION
CANDIDA ALBICANS 12X, 30X, 200X DETOXIFICATION
DL-MALIC ACID 6X,12X, 30X CELL METABOLISM
HYDROCOTYLE ASIATICA 6X CELL METABOLISM
MERCURIUS CORROSIVUS 6X CELL METABOLISM
MUCOR MUCEDO 12X, 30X, 200X DETOXIFICATION
NATRUM OXALACETICUM 6X,12X, 30X CELL METABOLISM
PINK TRUMPET TREE 4X DETOXIFICATION
SULPHUR 6X DETOXIFICATION

USES

Temporary relief of symptoms related to fungal yeast overgrowth in skin and mucosa, such as:

- Skin rashes
- Redness, itching
- Intestinal gas and bloating

WARNINGS

- Stop use and ask doctor if symptoms persist more than 5 days.
- If pregnant or breast-feeding ask a health professional before use.
- Keep out of reach of children. In case of overdose, get medical help or contact a Poison Control Center right away.
- Contains ethyl alcohol 30%

PREGNANCY

If pregnant or breast-feeding ask a doctor before use

WARNINGS

Keep out of reach of children

DIRECTIONS

Adults and children 12 years and older 20 drops in a little water, 2 times per day
Children between 12 years and 6 years of age 10 drops in a little water, 2 times per day
Children under 6 years 5 drops in a glass of water, 2 times per day

QUESTIONS

Questions?: info@gunainc.com, tel. (484) 223-3500

Inactive ingredient: Ethyl alcohol 30%.

INDICATIONS AND USAGE

Take 15 minutes before meals.